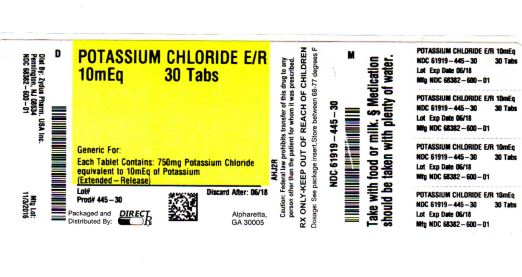 DRUG LABEL: POTASSIUM CHLORIDE
NDC: 61919-445 | Form: TABLET, FILM COATED, EXTENDED RELEASE
Manufacturer: DIRECT RX
Category: prescription | Type: HUMAN PRESCRIPTION DRUG LABEL
Date: 20200121

ACTIVE INGREDIENTS: POTASSIUM CHLORIDE 750 mg/1 1
INACTIVE INGREDIENTS: CASTOR OIL; SILICON DIOXIDE; D&C YELLOW NO. 10; MAGNESIUM STEARATE; PARAFFIN; TITANIUM DIOXIDE; VANILLIN; .ALPHA.-TOCOPHEROL; ETHYLCELLULOSES

POTASSIUM CHLORIDE

DESCRIPTION SECTION

Potassium chloride extended-release tablets is a solid oral dosage form of potassium chloride containing 10 mEq and 20 mEq of potassium chloride, USP, equivalent to 750 mg and 1500 mg of potassium in a film-coated (not enteric-coated), wax matrix tablet. These formulations are intended to slow the release of potassium so that the likelihood of a high localized concentration of potassium chloride within the gastrointestinal tract is reduced. The expended inert, porous, wax/polymer matrix is not absorbed and may be excreted intact in the stool.

Potassium chloride extended-release tablets are an electrolyte replenisher. The chemical name is potassium chloride, and the structural formula is KCl. Potassium chloride, USP, occurs as a white, granular powder or as colorless crystals. It is odorless and has a saline taste. Its solutions are neutral to litmus. It is freely soluble in water and insoluble in alcohol.

Inactive Ingredients

10 mEq Tablets

Castor oil, cellulosic polymers, colloidal silicon dioxide, D&C Yellow No. 10, magnesium stearate, paraffin, polyvinyl acetate, titanium dioxide, vanillin and vitamin E.

20 mEq Tablets

Castor oil, cellulosic polymers, colloidal silicon dioxide, magnesium stearate, paraffin, polyvinyl acetate, titanium dioxide, vanillin and vitamin E.

CLINICAL PHARMACOLOGY SECTION

Potassium ion is the principal intracellular cation of most body tissues. Potassium ions participate in a number of essential physiological processes including the maintenance of intracellular tonicity, the transmission of nerve impulses, the contraction of cardiac, skeletal and smooth muscle, and the maintenance of normal renal function.

The intracellular concentration of potassium is approximately 150 to 160 mEq per liter. The normal adult plasma concentration is 3.5 to 5 mEq per liter. An active ion transport system maintains this gradient across the plasma membrane.

Potassium is a normal dietary constituent and under steady state conditions the amount of potassium absorbed from the gastrointestinal tract is equal to the amount excreted in the urine. The usual dietary intake of potassium is 50 to 100 mEq per day.

Potassium depletion will occur whenever the rate of potassium loss through renal excretion and/or loss from the gastrointestinal tract exceeds the rate of potassium intake. Such depletion usually develops as a consequence of therapy with diuretics, primary or secondary hyperaldosteronism, diabetic ketoacidosis, or inadequate replacement of potassium in patients on prolonged parenteral nutrition. Depletion can develop rapidly with severe diarrhea, especially if associated with vomiting. Potassium depletion due to these causes is usually accompanied by a concomitant loss of chloride and is manifested by hypokalemia and metabolic alkalosis. Potassium depletion may produce weakness, fatigue, disturbances of cardiac rhythm (primarily ectopic beats), prominent U-waves in the electrocardiogram, and, in advanced cases, flaccid paralysis and/or impaired ability to concentrate urine.

If potassium depletion associated with metabolic alkalosis cannot be managed by correcting the fundamental cause of the deficiency, e.g., where the patient requires long term diuretic therapy, supplemental potassium in the form of high potassium food or potassium chloride may restore normal potassium levels.

In rare circumstances, (e.g., patients with renal tubular acidosis) potassium depletion may be associated with metabolic acidosis and hyperchloremia. In such patients potassium replacement should be accomplished with potassium salts other than the chloride, such as potassium bicarbonate, potassium citrate, potassium acetate, or potassium gluconate.

INDICATIONS & USAGE SECTION

BECAUSE OF REPORTS OF INTESTINAL AND GASTRIC ULCERATION AND BLEEDING WITH CONTROLLED-RELEASE POTASSIUM CHLORIDE PREPARATIONS, THESE DRUGS SHOULD BE RESERVED FOR THOSE PATIENTS WHO CANNOT TOLERATE OR REFUSE TO TAKE LIQUID OR EFFERVESCENT POTASSIUM PREPARATIONS, OR FOR PATIENTS WITH WHOM THERE IS A PROBLEM OF COMPLIANCE WITH THESE PREPARATIONS.

1. For the treatment of patients with hypokalemia with or without metabolic alkalosis, in digitalis intoxication, and in patients with hypokalemic familial periodic paralysis. If hypokalemia is the result of diuretic therapy, consideration should be given to the use of a lower dose of diuretic, which may be sufficient without leading to hypokalemia.
2. For the prevention of hypokalemia in patients who would be at particular risk if hypokalemia were to develop, e.g., digitalized patients or patients with significant cardiac arrhythmias.

The use of potassium salts in patients receiving diuretics for uncomplicated essential hypertension is often unnecessary when such patients have a normal dietary pattern, and when low doses of the diuretic are used. Serum potassium should be checked periodically, however, and, if hypokalemia occurs, dietary supplementation with potassium-containing foods may be adequate to control milder cases. In more severe cases and if dose adjustment of the diuretic is ineffective or unwarranted supplementation with potassium salts may be indicated.

CONTRAINDICATIONS SECTION

Potassium supplements are contraindicated in patients with hyperkalemia since a further increase in serum potassium concentration in such patients can produce cardiac arrest. Hyperkalemia may complicate any of the following conditions: chronic renal failure, systemic acidosis such as diabetic acidosis, acute dehydration, extensive tissue breakdown as in severe burns, adrenal insufficiency, or the administration of a potassium-sparing diuretic, e.g., spironolactone, triamterene, or amiloride (see OVERDOSAGE).

Potassium chloride extended-release tablets are contraindicated in patients with known hypersensitivity to any ingredient in this product.

Controlled-release formulations of potassium chloride have produced esophageal ulceration in certain cardiac patients with esophageal compression due to an enlarged left atrium. Potassium supplementation, when indicated in such patients, should be given as a liquid preparation.

All solid oral dosage forms of potassium chloride are contraindicated in any patient in whom there is structural, pathological, e.g., diabetic gastroparesis, or pharmacologic (use of anticholinergic agents or other agents with anticholinergic properties at sufficient doses to exert anticholinergic effects) cause for arrest or delay in tablet passage through the gastrointestinal tract.

WARNINGS SECTION

Hyperkalemia (see OVERDOSAGE)

In patients with impaired mechanisms for excreting potassium, the administration of potassium salts can produce hyperkalemia and cardiac arrest. This occurs most commonly in patients given potassium intravenously, but may also occur in patients given potassium orally. Potentially fatal hyperkalemia can develop rapidly and can be asymptomatic. The use of potassium salts in patients with chronic renal disease, or any other condition which impairs potassium excretion, requires particularly careful monitoring of the serum potassium concentration and appropriate dosage adjustment.

Interaction with Potassium-Sparing Diuretics

Hypokalemia should not be treated by the concomitant administration of potassium salts and a potassium-sparing diuretic, e.g., spironolactone, triamterene, or amiloride, since the simultaneous administration of these agents can produce severe hyperkalemia.

Interaction with Angiotensin Converting Enzyme Inhibitors

Angiotensin converting enzyme (ACE) inhibitors (e.g., captopril, enalapril) will produce some potassium retention by inhibiting aldosterone production. Potassium supplements should be given to patients receiving ACE inhibitors only with close monitoring.

Gastrointestinal Lesions

Solid oral dosage forms of potassium chloride can produce ulcerative and/or stenotic lesions of the gastrointestinal tract. Based on spontaneous adverse reaction reports, enteric-coated preparations of potassium chloride are associated with an increased frequency of small bowel lesions (40-50 per 100,000 patient years) compared to sustained-release wax matrix formulations (less than one per 100,000 patient years). Because of the lack of extensive marketing experience with microencapsulated products, a comparison between such products and wax matrix or enteric-coated products is not available. Potassium chloride extended-release tablets consist of a wax matrix formulated to provide a controlled rate of release potassium chloride and thus to minimize the possibility of a high local concentration of potassium near the gastrointestinal wall.

Prospective trials have been conducted in normal human volunteers in which the upper gastrointestinal tract was evaluated by endoscopic inspection before and after one week of solid oral potassium chloride therapy. The ability of this model to predict events occurring in usual clinical practice is unknown. Trials which approximated usual clinical practice did not reveal any clear differences between the wax matrix and microencapsulated dosage forms. In contrast, there was a higher incidence of gastric and duodenal lesions in subjects receiving a high dose of a wax matrix controlled-release formulation under conditions which did not resemble usual or recommended clinical practice, i.e., 96 mEq per day in divided doses of potassium chloride administered, to fasted patients in the presence of an anticholinergic drug to delay gastric emptying. The upper gastrointestinal lesions observed by endoscopy were asymptomatic and were not accompanied by evidence of bleeding (hemoccult testing). The relevance of these findings to the usual conditions, i.e., nonfasting, no anticholinergic agent, and smaller doses, under which controlled-release potassium chloride products are used is uncertain. Epidemiologic studies have not identified an elevated risk, compared to microencapsulated products, for upper gastrointestinal lesions in patients receiving wax matrix formulations. Potassium chloride extended-release tablets should be discontinued immediately and the possibility of ulceration, obstruction or perforation considered if severe vomiting, abdominal pain, distention, or gastrointestinal bleeding occurs.

Metabolic Acidosis

Hypokalemia in patients with metabolic acidosis should be treated with an alkalinizing potassium salt such as potassium bicarbonate, potassium citrate, potassium acetate, or potassium gluconate.

PRECAUTIONS SECTION

General

The diagnosis of potassium depletion is ordinarily made by demonstrating hypokalemia in a patient with a clinical history suggesting some cause for potassium depletion. In interpreting the serum potassium level, the physician should bear in mind that acute alkalosis per se can produce hypokalemia in the absence of a deficit in total body potassium, while acute acidosis per se can increase the serum potassium concentration to within the normal range even in the presence of a reduced total body potassium. The treatment of potassium depletion, particularly in the presence of cardiac disease, renal disease, or acidosis, requires careful attention to acid-base balance and appropriate monitoring of serum electrolytes, the electrocardiogram, and the clinical status of the patient.

Information for Patients

Physicians should consider reminding the patient of the following:

To take each dose with meals and with a full glass of water or other liquid.

To take this medicine following the frequency and amount prescribed by the physician. This is especially important if the patient is also taking diuretics and/or digitalis preparations.

To check with the physician if there is trouble swallowing tablets or if the tablets seem to stick in the throat.

To check with the physician at once if tarry stools or other evidence of gastrointestinal bleeding is noticed.

To take each dose without crushing, chewing or sucking the tablets.

Laboratory Tests

When blood is drawn for analysis of plasma potassium it is important to recognize that artifactual elevations can occur after improper venipuncture technique or as a result of in vitro hemolysis of the sample.

Drug Interactions

Potassium-sparing diuretics, angiotensin converting enzyme inhibitors (see WARNINGS).

Carcinogenesis, Mutagenesis, Impairment of Fertility

Carcinogenicity, mutagenicity and fertility studies in animals have not been performed. Potassium is a normal dietary constituent.

Pregnancy Category C

Animal reproduction studies have not been conducted with Potassium chloride extended-release tablets. It is unlikely that potassium supplementation that does not lead to hyperkalemia would have an adverse effect on the fetus or would affect reproductive capacity.

Nursing Mothers

The normal potassium ion content of human milk is about 13 mEq per liter. Since oral potassium becomes part of the body potassium pool, as long as body potassium is not excessive, the contribution of potassium chloride supplementation should have little or no effect on the level in human milk.

Pediatric Use

Safety and effectiveness in children have not been established.

Geriatric Use

Clinical Studies of Potassium chloride extended-release tablets did not include sufficient numbers of subjects aged 65 and over to determine whether they respond differently from younger subjects. Other reported clinical experience has not identified differences in responses between the elderly and younger patients. In general, dose selection for an elderly patient should be cautious, usually starting at the low end of the dosing range, reflecting the greater frequency of decreased hepatic, renal or cardiac function, and of concomitant disease or other drug therapy.

This drug is known to be substantially excreted by the kidney, and the risk of toxic reactions to this drug may be greater in patients with impaired renal function. Because elderly patients are more likely to have decreased renal function, care should be taken in dose selection, and it may be useful to monitor renal function.

ADVERSE REACTIONS SECTION

One of the most severe adverse effects is hyperkalemia (see CONTRAINDICATIONS, WARNINGS, and OVERDOSAGE). There also have been reports of upper and lower gastrointestinal conditions including obstruction, bleeding, ulceration, and perforation (see CONTRAINDICATIONS and WARNINGS).

The most common adverse reactions to oral potassium salts are nausea, vomiting, flatulence, abdominal pain/discomfort, and diarrhea. These symptoms are due to irritation of the gastrointestinal tract and are best managed by taking the dose with meals, or reducing the amount taken at one time.

Skin rash has been reported rarely.

OVERDOSAGE SECTION

The administration of oral potassium salts to persons with normal excretory mechanisms for potassium rarely causes serious hyperkalemia. However, if excretory mechanisms are impaired or if intravenous administration is too rapid, potentially fatal hyperkalemia can result (see CONTRAINDICATIONS and WARNINGS). It is important to recognize that hyperkalemia is usually asymptomatic and may be manifested only by an increased serum potassium concentration (6.5-8.0 mEq/L) and characteristic electrocardiographic changes (peaking of T-waves, loss P-waves, depression of S-T segments, and prolongation of the QT intervals). Late manifestations include muscle paralysis and cardiovascular collapse from cardiac arrest (9-12 mEq/L).

Treatment measures for hyperkalemia include the following:

1. Elimination of foods and medications containing potassium and of any agents with potassium-sparing properties;
2. Intravenous administration of 300 to 500 mL/hr of 10% dextrose solution containing 10-20 units of crystalline insulin per 1,000 mL;
3. Correction of acidosis, if present, with intravenous sodium bicarbonate;
4. Use of exchange resins, hemodialysis, or peritoneal dialysis.

In treating hyperkalemia, it should be recalled that in patients who have been stabilized on digitalis, lowering the serum potassium concentration too rapidly can produce digitalis toxicity.

The extended release feature means that absorption and toxic effects may be delayed for hours. Consider standard measures to remove any unabsorbed drug.

DOSAGE & ADMINISTRATION SECTION

The usual dietary potassium intake by the average adult is 50 to 100 mEq per day. Potassium depletion sufficient to cause hypokalemia usually requires the loss of 200 or more mEq of potassium from the total body store.

Dosage must be adjusted to the individual needs of each patient. The dose for the prevention of hypokalemia is typically in the range of 20 mEq per day. Doses of 40-100 mEq per day or more are used for the treatment of potassium depletion. Dosage should be divided if more than 20 mEq per day is given such that no more than 20 mEq is given in a single dose.

Potassium chloride extended-release tablets provide 10 mEq and 20 mEq of potassium chloride.

Potassium chloride extended-release tablets should be taken with meals and with a glass of water or other liquid. This product should not be taken on an empty stomach because of its potential for gastric irritation (see WARNINGS).

NOTE:Potassium chloride extended-release tablets are to be swallowed whole without crushing, chewing or sucking the tablets.

HOW SUPPLIED SECTION

Potassium chloride extended-release tablets, USP contain 750 mg and 1500 mg of potassium chloride (equivalent to 10 mEq and 20 mEq, respectively). Potassium chloride extended-release tablets, USP are provided as ovaloid, extended-release, film-coated tablets. Potassium chloride extended-release tablets 750 mg are yellow in color and are debossed with the “a” logo on one side and the trademark K-TAB on the other side. Potassium chloride extended-release tablets 1500 mg are white in color and are debossed with the trademark K-TAB on one side.

Potassium chloride extended-release tablets are supplied as follows:

10 mEq

Bottles of 30 | NDC 68382-600-06
Bottles of 90 | NDC 68382-600-16
Bottles of 100 | NDC 68382-600-01
Bottles of 1000 | NDC 68382-600-10

20 mEq

Bottles of 30 | NDC 68382-398-06
Bottles of 90 | NDC 68382-398-16
Bottles of 100 | NDC 68382-398-01
Bottles of 500 | NDC 68382-398-05

Recommended Storage

Do not store above 77°F (25°C).

Manufactured by:

AbbVie LTD

Barceloneta, PR 00617

Distributed by:

Zydus Pharmaceuticals USA Inc.

Pennington, NJ 08534

03-A826 November, 2013

NDC 68382–600–01

ZyGenerics

POTASSIUM CHLORIDE EXTENDED— RELEASE TABLETS, USP

10 mEq (750 mg) 100 Film-Coated Tablets